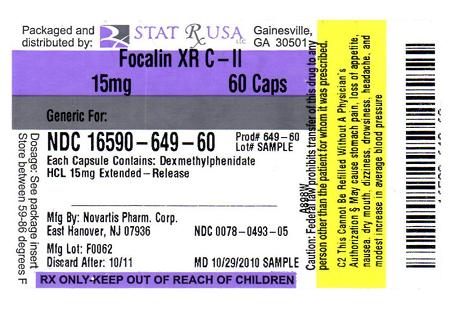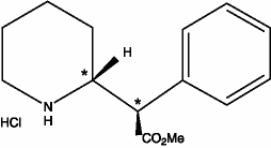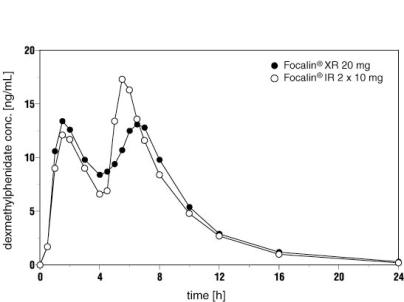 DRUG LABEL: FOCALIN 
NDC: 16590-649 | Form: CAPSULE, EXTENDED RELEASE
Manufacturer: STAT RX USA LLC
Category: prescription | Type: HUMAN PRESCRIPTION DRUG LABEL
Date: 20110613
DEA Schedule: CII

ACTIVE INGREDIENTS: DEXMETHYLPHENIDATE HYDROCHLORIDE 15 mg/1 1
INACTIVE INGREDIENTS: FD&C BLUE NO. 2; FERRIC OXIDE YELLOW; GELATIN; POLYETHYLENE GLYCOL; DEXTROSE; TALC; TITANIUM DIOXIDE; TRIETHYL CITRATE

HIGHLIGHTS OF PRESCRIBING INFORMATION

These highlights do not include all the information needed to use FOCALIN XR safely and effectively. See full prescribing information for FOCALIN XR.
FOCALIN XR (dexmethylphenidate hydrochloride) Extended-Release Capsules CII for oral use
Initial U.S. Approval: 2005

WARNING: DRUG DEPENDENCE

See full prescribing information for complete boxed warning

Focalin XR should be given cautiously to patients with a history of drug dependence or alcoholism. Chronic abusive use can lead to marked tolerance and psychological dependence, with varying degrees of abnormal behavior.

1 INDICATIONS AND USAGE

Focalin XR is a CNS stimulant indicated for the treatment of Attention Deficit Hyperactivity Disorder (ADHD) in patients aged 6 years and older (1)

2 DOSAGE AND ADMINISTRATION

- Focalin XR is intended for oral administration once daily in the morning. Focalin XR capsules may be swallowed whole, or capsule contents can be sprinkled on applesauce. Focalin XR and/or their contents should not be crushed, chewed, or divided (2)
- For patients new to methylphenidate: Begin treatment with Focalin XR at 5 mg/day for pediatrics and 10 mg/day for adults, titrating the dose weekly in 5 mg increments for pediatrics and in 10 mg increments for adults. Doses above 30 mg/day in children and 40 mg/day in adults have not been studied. (2.1)
- For patients already using methylphenidate: Initiate Focalin XR therapy with half (1/2) the current total daily dose of methylphenidate. (2.2)
- Patients already using Focalin (dexmethylphenidate) immediate release: switch to the same daily dose of Focalin XR. (2.2)

3 DOSAGE FORMS AND STRENGTHS

Extended-release capsules: 5, 10, 15, 20, 25, 30, 35, and 40 mg

4 CONTRAINDICATIONS

- Agitation, marked anxiety, and tension (4.1)
- Known hypersensitivity to methylphenidate or product components (4.2)
- Glaucoma (4.3)
- History of motor tics or a family history or diagnosis of Tourette’s syndrome (4.4)
- During, or within a minimum of 14 days following discontinuation of treatment with a monoamine oxidase inhibitor (MAOI) (4.5)

5 WARNINGS AND PRECAUTIONS

- Serious Cardiovascular Events: Sudden death has been reported in association with CNS stimulant treatment at usual doses in children and adolescents with structural cardiac abnormalities or other serious heart problems. Sudden death, stroke, and myocardial infarction have been reported in adults taking stimulant drugs at usual doses for ADHD. Stimulant products generally should not be used in patients with known structural cardiac abnormalities, cardiomyopathy, serious heart rhythm abnormalities, coronary artery disease, or other serious heart problems. (5.1)
- Increased Blood Pressure and Heart Rate: have been reported. Monitor patients for changes in blood pressure and heart rate. Caution should be exercised in treating patients whose underlying medical conditions might be compromised by increases in blood pressure or heart rate (5.2)
- Assess Cardiovascular Status: prior to stimulant treatment, assess for cardiac disease with history and exam and, if suggested by findings, conduct further cardiac evaluation. Patients with emerging symptoms suggestive of cardiac disease should undergo a prompt cardiac evaluation (5.3)
- Psychotic Symptoms: may be exacerbated in patients with psychotic disorders (5.4)
- Bipolar Disorder: Use with particular care in ADHD patients with comorbid Bipolar Disorder. Before initiating stimulant therapy, obtain a detailed psychiatric history for patients with comorbid depressive symptoms, in order to determine risk for Bipolar Disorder. (5.5)
- Emergence of New Psychotic or Manic Symptoms: Treatment-emergent psychotic or manic symptoms without a prior history can be caused by stimulants at usual doses. Discontinuation of stimulant therapy may be indicated (5.6)
- Aggression: Monitor for appearance of or worsening of aggressive behavior or hostility (5.7)
- Long-Term Suppression of Growth: monitor height and weight in pediatric patients at appropriate intervals. Patients who are not growing or gaining weight as expected may need to have their treatment interrupted (5.8)
- Seizures: The threshold for seizures may be lowered. In the presence of seizure, discontinue treatment. (5.9)
- Visual Disturbance: difficulties with accommodation and blurring of vision have been reported with stimulant treatment (5.10)
- Hematologic Monitoring: periodic monitoring of CBC with differential is advised during prolonged therapy (5.12)

6 ADVERSE REACTIONS

Most common adverse reactions (at least 5% and twice the incidence among placebo-treated patients) are dyspepsia, decreased appetite, headache, and anxiety for pediatric patients and dry mouth, dyspepsia, headache, and anxiety for adult patients (6).

To report SUSPECTED ADVERSE REACTIONS, contact Novartis Pharmaceuticals Corporation at 1-888-669-6682 or FDA at 1-800-FDA-1088 or www.fda.gov/medwatch.

7 DRUG INTERACTIONS

- Focalin XR should not be used in patients being treated (currently or within the preceding two weeks) with MAO Inhibitors (4.5)
- Focalin XR should be used cautiously with pressor agents (7)
- Antacids or acid suppressants could alter the release of Focalin XR (7)
- Racemic methylphenidate may inhibit the metabolism of coumarin anticoagulants, anticonvulsants, and tricyclic drugs (7)

8 USE IN SPECIFIC POPULATIONS

- Focalin XR should not be used in children under 6 years of age (5.11)
- Pregnancy: Limited human data. Based on animal data, may cause fetal harm (8.1).
- Nursing Mothers: Caution should be exercised when administered to a nursing woman (8.3).

FULL PRESCRIBING INFORMATION

WARNING: DRUG DEPENDENCE

Focalin XR should be given cautiously to patients with a history of drug dependence or alcoholism. Chronic abusive use can lead to marked tolerance and psychological dependence with varying degrees of abnormal behavior. Frank psychotic episodes can occur, especially with parenteral abuse. Careful supervision is required during withdrawal from abusive use, since severe depression may occur. Withdrawal following chronic therapeutic use may unmask symptoms of the underlying disorder that may require follow-up.

1 INDICATIONS AND USAGE

Focalin XR is indicated for the treatment of Attention Deficit Hyperactivity Disorder (ADHD) in patients aged 6 years and older.

The effectiveness of Focalin XR in the treatment of ADHD in patients aged 6 years and older was established in two placebo-controlled studies in patients meeting DSM-IV criteria for ADHD [see Clinical Studies (14)].

A diagnosis of Attention Deficit Hyperactivity Disorder (ADHD; DSM-IV) implies the presence of hyperactive-impulsive or inattentive symptoms that caused impairment and were present before age 7 years. The symptoms must cause clinically significant impairment, e.g., in social, academic, or occupational functioning, and be present in two or more settings, e.g., school (or work) and at home. The symptoms must not be better accounted for by another mental disorder. For the Inattentive Type, at least six of the following symptoms must have persisted for at least 6 months: lack of attention to details/careless mistakes; lack of sustained attention; poor listener; failure to follow through on tasks; poor organization; avoids tasks requiring sustained mental effort; loses things; easily distracted; forgetful. For the Hyperactive-Impulsive Type, at least six of the following symptoms must have persisted for at least 6 months: fidgeting/squirming; leaving seat; inappropriate running/climbing; difficulty with quiet activities; “on the go”; excessive talking; blurting answers; can’t wait turn; intrusive. The Combined Types requires both inattentive and hyperactive-impulsive criteria to be met.

Special Diagnostic Considerations

Specific etiology of this syndrome is unknown, and there is no single diagnostic test. Adequate diagnosis requires the use not only of medical but of special psychological, educational, and social resources. Learning may or may not be impaired. The diagnosis must be based upon a complete history and evaluation of the child and not solely on the presence of the required number of DSM-IV characteristics.

Need for Comprehensive Treatment Program

Focalin XR is indicated as an integral part of a total treatment program for ADHD that may include other measures (psychological, educational, social) for patients with this syndrome. Drug treatment may not be indicated for all children with this syndrome. Stimulants are not intended for use in the child who exhibits symptoms secondary to environmental factors and/or other primary psychiatric disorders, including psychosis. Appropriate educational placement is essential and psychosocial intervention is often helpful. When remedial measures alone are insufficient, the decision to prescribe stimulant medication will depend upon the physician’s assessment of the chronicity and severity of the child’s symptoms.

Long-Term Use

The effectiveness of Focalin XR for long-term use, i.e., for more than 7 weeks, has not been systematically evaluated in controlled trials. Therefore, the physician who elects to use Focalin XR for extended periods should periodically reevaluate the long-term usefulness of the drug for the individual patient [see Dosage and Administration (2.3)].

2 DOSAGE AND ADMINISTRATION

Focalin XR is for oral administration once daily in the morning.

Focalin XR may be swallowed as whole capsules or alternatively may be administered by sprinkling the capsule contents on a small amount of applesauce (see specific instructions below). Focalin XR and/or their contents should not be crushed, chewed, or divided.

The capsules may be carefully opened and the beads sprinkled over a spoonful of applesauce. The mixture of drug and applesauce should be consumed immediately in its entirety. The drug and applesauce mixture should not be stored for future use.

Dosage should be individualized according to the needs and responses of the patient.

2.1 Patients New to Methylphenidate

The recommended starting dose of Focalin XR for patients who are not currently taking dexmethylphenidate or racemic methylphenidate, or for patients who are on stimulants other than methylphenidate, is 5 mg/day for pediatric patients and 10 mg/day for adult patients.

Dosage may be adjusted in 5 mg increments for pediatric patients and in 10 mg increments for adult patients. In general, dosage adjustments may proceed at approximately weekly intervals. The patient should be observed for a sufficient duration at a given dose to ensure that a maximal benefit has been achieved before a dose increase is considered. In dose-response (fixed-dose) studies (pediatric from 10 to 30 mg/day and adult from 20 to 40 mg/day), all doses were effective vs. placebo. There was no clear finding, however, of greater average benefits for the higher doses compared to the lower doses. Adverse events and discontinuations, however, were dose-related. Doses above 30 mg/day in pediatrics and 40 mg/day in adults have not been studied and are not recommended.

2.2 Patients Currently Using Methylphenidate

For patients currently using methylphenidate, the recommended starting dose of Focalin XR is half the total daily dose of racemic methylphenidate. Patients currently using Focalin (dexmethylphenidate) may be switched to the same daily dose of Focalin XR.

2.3 Maintenance/Extended Treatment

There is no body of evidence available from controlled trials to indicate how long the patient with ADHD should be treated with Focalin XR. It is generally agreed, however, that pharmacological treatment of ADHD may be needed for extended periods. Nevertheless, the physician who elects to use Focalin XR for extended periods in patients with ADHD should periodically reevaluate the long-term usefulness of the drug for the individual patient with periods off medication to assess the patient’s functioning without pharmacotherapy. Improvement may be sustained when the drug is either temporarily or permanently discontinued.

2.4 Dose Reduction and Discontinuation

If paradoxical aggravation of symptoms or other adverse events occur, the dosage should be reduced, or, if necessary, the drug should be discontinued.

If improvement is not observed after appropriate dosage adjustment over a 1-month period, the drug should be discontinued.

3 DOSAGE FORMS AND STRENGTHS

5 mg extended-release capsules

10 mg extended-release capsules

15 mg extended-release capsules

20 mg extended-release capsules

25 mg extended-release capsules

30 mg extended-release capsules

35 mg extended-release capsules

40 mg extended-release capsules

4 CONTRAINDICATIONS

4.1 Agitation

Focalin XR is contraindicated in patients with marked anxiety, tension, and agitation, since the drug may aggravate these symptoms.

4.2 Hypersensitivity to Methylphenidate

Focalin XR is contraindicated in patients known to be hypersensitive to methylphenidate, or other components of the product.

4.3 Glaucoma

Focalin XR is contraindicated in patients with glaucoma.

4.4 Tics

Focalin XR is contraindicated in patients with motor tics or with a family history or diagnosis of Tourette’s syndrome [see Adverse Reactions (6.1)].

4.5 Monoamine Oxidase Inhibitors

Focalin XR is contraindicated during treatment with monoamine oxidase inhibitors, and also within a minimum of 14 days following discontinuation of treatment with a monoamine oxidase inhibitor (hypertensive crises may result).

5 WARNINGS AND PRECAUTIONS

5.1 Sudden Death and Pre-Existing Structural Cardiac Abnormalities or Other Serious Heart Problems

Children and Adolescents

Sudden death has been reported in association with CNS stimulant treatment at usual doses in children and adolescents with structural cardiac abnormalities or other serious heart problems. Although some serious heart problems alone carry an increased risk of sudden death, stimulant products generally should not be used in children or adolescents with known serious structural cardiac abnormalities, cardiomyopathy, serious heart rhythm abnormalities, or other serious cardiac problems that may place them at increased vulnerability to the sympathomimetic effects of a stimulant drug.

Adults

Sudden death, stroke, and myocardial infarction have been reported in adults taking stimulant drugs at usual doses for ADHD. Although the role of stimulants in these adult cases is also unknown, adults have a greater likelihood than children of having serious structural cardiac abnormalities, cardiomyopathy, serious heart rhythm abnormalities, coronary artery disease, or other serious cardiac problems. Adults with such abnormalities should also generally not be treated with stimulant drugs.

5.2 Hypertension and other Cardiovascular Conditions

Stimulant medications cause a modest increase in average blood pressure (about 2-4 mmHg) and average heart rate (about 3-6 bpm), and individuals may have larger increases. While the mean changes alone would not be expected to have short-term consequences, all patients should be monitored for larger changes in heart rate and blood pressure. Caution is indicated in treating patients whose underlying medical conditions might be compromised by increases in blood pressure or heart rate, e.g., those with pre-existing hypertension, heart failure, recent myocardial infarction, or ventricular arrhythmia.

5.3 Assessing Cardiovascular Status in Patients being Treated with Stimulant Medications

Children, adolescents, or adults who are being considered for treatment with stimulant medications should have a careful history (including assessment for a family history of sudden death or ventricular arrhythmia) and physical exam to assess for the presence of cardiac disease, and should receive further cardiac evaluation if findings suggest such disease (e.g., electrocardiogram and echocardiogram). Patients who develop symptoms such as exertional chest pain, unexplained syncope, or other symptoms suggestive of cardiac disease during stimulant treatment should undergo a prompt cardiac evaluation.

5.4 Pre-Existing Psychosis

Administration of stimulants may exacerbate symptoms of behavior disturbance and thought disorder in patients with a pre-existing psychotic disorder.

5.5 Bipolar Illness

Particular care should be taken in using stimulants to treat ADHD in patients with comorbid bipolar disorder because of concern for possible induction of a mixed/manic episode in such patients. Prior to initiating treatment with a stimulant, patients with comorbid depressive symptoms should be adequately screened to determine if they are at risk for bipolar disorder; such screening should include a detailed psychiatric history, including a family history of suicide, bipolar disorder, and depression.

5.6 Emergence of New Psychotic or Manic Symptoms

Treatment emergent psychotic or manic symptoms, e.g., hallucinations, delusional thinking, or mania in children and adolescents without a prior history of psychotic illness or mania can be caused by stimulants at usual doses. If such symptoms occur, consideration should be given to a possible causal role of the stimulant, and discontinuation of treatment may be appropriate. In a pooled analysis of multiple short-term, placebo-controlled studies, such symptoms occurred in about 0.1% (4 patients with events out of 3,482 exposed to methylphenidate or amphetamine for several weeks at usual doses) of stimulant-treated patients compared to 0 in placebo-treated patients.

5.7 Aggression

Aggressive behavior or hostility is often observed in children and adolescents with ADHD, and has been reported in clinical trials and the post marketing experience of some medications indicated for the treatment of ADHD. Although there is no systematic evidence that stimulants cause aggressive behavior or hostility, patients beginning treatment for ADHD should be monitored for the appearance of or worsening of aggressive behavior or hostility.

5.8 Long-Term Suppression of Growth

Careful follow-up of weight and height in children ages 7 to 10 years who were randomized to either methylphenidate or non-medication treatment groups over 14 months, as well as in naturalistic subgroups of newly methylphenidate-treated and non-medication treated children over 36 months (to the ages of 10 to 13 years), suggests that consistently medicated children (i.e., treatment for 7 days per week throughout the year) have a temporary slowing in growth rate (on average, a total of about 2 cm less growth in height and 2.7 kg less growth in weight over 3 years), without evidence of growth rebound during this period of development. In the 7-week double-blind placebo-controlled study of Focalin XR, the mean weight gain was greater for patients receiving placebo (+0.4 kg) than for patients receiving Focalin XR (-0.5 kg). Published data are inadequate to determine whether chronic use of amphetamines may cause a similar suppression of growth, however, it is anticipated that they likely have this effect as well. Therefore, growth should be monitored during treatment with stimulants, and patients who are not growing or gaining height or weight as expected may need to have their treatment interrupted.

5.9 Seizures

There is some clinical evidence that stimulants may lower the convulsive threshold in patients with prior history of seizures, in patients with prior EEG abnormalities in absence of seizures, and, very rarely, in patients without a history of seizures and no prior EEG evidence of seizures. In the presence of seizures, the drug should be discontinued.

5.10 Visual Disturbance

Difficulties with accommodation and blurring of vision have been reported with stimulant treatment.

5.11 Use in Children Under Six Years of Age

Focalin XR should not be used in children under 6 years of age, since safety and efficacy in this age group have not been established.

5.12 Hematologic Monitoring

Periodic CBC, differential, and platelet counts are advised during prolonged therapy.

6 ADVERSE REACTIONS

Focalin XR was administered to 46 children and 7 adolescents with ADHD for up to 7 weeks and 206 adults with ADHD in clinical studies. During the clinical studies, 101 adult patients were treated for at least 6 months.

Adverse events during exposure were obtained primarily by general inquiry and recorded by clinical investigators using terminology of their own choosing. Consequently, it is not possible to provide a meaningful estimate of the proportion of individuals experiencing adverse events without first grouping similar types of events into a smaller number of standardized event categories. In the tables and listings that follow, MedDRA terminology has been used to classify reported adverse events. The stated frequencies of adverse events represent the proportion of individuals who experienced, at least once, a treatment-emergent adverse event of the type listed. An event was considered treatment emergent if it occurred for the first time or worsened while receiving therapy following baseline evaluation.

6.1 Adverse Events Associated with Discontinuation of Treatment in Acute Clinical Studies with Focalin XR - Children

Overall, 50 of 684 children treated with Focalin immediate-release formulation (7.3%) experienced an adverse event that resulted in discontinuation. The most common reasons for discontinuation were twitching (described as motor or vocal tics), anorexia, insomnia, and tachycardia (approximately 1% each). None of the 53 Focalin XR-treated pediatric patients discontinued treatment due to adverse events in the 7-week placebo-controlled study.

6.2 Adverse Events Occurring at an Incidence of 5% or More Among Focalin XR-Treated Patients-Children

Table 1 enumerates treatment-emergent adverse events for the placebo-controlled, parallel-group study in children and adolescents with ADHD at flexible Focalin XR doses of 5-30 mg/day. The table includes only those events that occurred in 5% or more of patients treated with Focalin XR and for which the incidence in patients treated with Focalin XR was at least twice the incidence in placebo-treated patients. The prescriber should be aware that these figures cannot be used to predict the incidence of adverse events in the course of usual medical practice where patient characteristics and other factors differ from those which prevailed in the clinical trials. Similarly, the cited frequencies cannot be compared with figures obtained from other clinical investigations involving different treatments, uses, and investigators. The cited figures, however, do provide the prescribing physician with some basis for estimating the relative contribution of drug and non-drug factors to the adverse event incidence rate in the population studied.

Table 1.Treatment-Emergent Adverse Events^1 Occurring During Double-Blind Treatment–Pediatric Patients
 | Focalin XR N=53 | Placebo N=47
No. of Patients with AEs
Total | 76% | 57%
Primary System Organ Class/ Adverse Event Preferred Term
Gastrointestinal Disorders | 38% | 19%
Dyspepsia | 8% | 4%
Metabolism and Nutrition Disorders | 34% | 11%
Decreased Appetite | 30% | 9%
Nervous System Disorders | 30% | 13%
Headache | 25% | 11%
Psychiatric Disorders | 26% | 15%
Anxiety | 6% | 0%

^1Events, regardless of causality, for which the incidence for patients treated with Focalin XR was at least 5% and twice the incidence among placebo-treated patients. Incidence has been rounded to the nearest whole number.

Table 2 below enumerates the incidence of dose-related adverse events that occurred during a fixed-dose, double-blind, placebo controlled trial of Focalin XR up to 30mg/day versus placebo in children and adolescents with ADHD.

Table 2: Dose-related Adverse Events from a Fixed-dose Study of Double-Blind Treatment in Pediatric Patients By Organ-System and Preferred Term
ADVERSE EVENT | Focalin XR 10 mg/d N=64 | Focalin XR 20 mg/d N=60 | Focalin XR 30 mg/d N=58 | Placebo N=63
Gastrointestinal disorders | 22% | 23% | 29% | 24%
Vomiting | 2% | 8% | 9% | 0
Metabolism and nutritional disorders | 16% | 17% | 22% | 5%
Anorexia | 5% | 5% | 7% | 0
Psychiatric Disorders | 19% | 20% | 38% | 8%
Insomnia | 5% | 8% | 17% | 3%
Depression | 0 | 0 | 3% | 0
Mood swings | 0 | 0 | 3% | 2%
Other Adverse events
Irritability | 0 | 2% | 5% | 0
Nasal Congestion | 0 | 0 | 5% | 0
Pruritus | 0 | 0 | 3% | 0

6.3 Adverse Events Associated with Discontinuation of Treatment in Clinical Studies with Focalin XR - Adults

In the adult placebo-controlled study, 10.7% of the Focalin XR-treated patients and 7.5% of the placebo-treated patients discontinued for adverse events. Among Focalin XR-treated patients, insomnia (1.8%, n=3), feeling jittery (1.8%, n=3), anorexia (1.2%, n=2), and anxiety (1.2%, n=2) were the reasons for discontinuation reported by more than 1 patient.

6.4 Adverse Events Occurring at an Incidence of 5% or More Among Focalin XR-Treated Patients-Adults

Table 3 enumerates treatment-emergent adverse events for the placebo-controlled, parallel-group study in adults with ADHD at fixed Focalin XR doses of 20, 30, and 40 mg/day. The table includes only those events that occurred in 5% or more of patients in a Focalin XR dose group and for which the incidences in patients treated with Focalin XR appeared to increase with dose. The prescriber should be aware that these figures cannot be used to predict the incidence of adverse events in the course of usual medical practice where patient characteristics and other factors differ from those which prevailed in the clinical trials. Similarly, the cited frequencies cannot be compared with figures obtained from other clinical investigations involving different treatments, uses, and investigators. The cited figures, however, do provide the prescribing physician with some basis for estimating the relative contribution of drug and non-drug factors to the adverse event incidence rate in the population studied.

Table 3. Treatment-Emergent Adverse Events1 Occurring During Double-Blind Treatment–Adults
 | Focalin XR 20 mg N=57 | Focalin XR 30 mg N=54 | Focalin XR 40 mg N=54 | Placebo N=53
No. of Patients with AEs
Total | 84% | 94% | 85% | 68%
Primary System Organ Class/ Adverse Event Preferred Term
Gastrointestinal Disorders | 28% | 32% | 44% | 19%
Dry Mouth | 7% | 20% | 20% | 4%
Dyspepsia | 5% | 9% | 9% | 2%
Nervous System Disorders | 37% | 39% | 50% | 28%
Headache | 26% | 30% | 39% | 19%
Psychiatric Disorders | 40% | 43% | 46% | 30%
Anxiety | 5% | 11% | 11% | 2%
Respiratory, Thoracic and Mediastinal Disorders | 16% | 9% | 15% | 8%
Pharyngolaryngeal Pain | 4% | 4% | 7% | 2%

^1Events, regardless of causality, for which the incidence was at least 5% in a Focalin XR group and which appeared to increase with randomized dose. Incidence has been rounded to the nearest whole number.

Two other adverse reactions occurring in clinical trials with Focalin XR at a frequency greater than placebo, but which were not dose related were: Feeling jittery (12% and 2%, respectively) and Dizziness (6% and 2%, respectively).

Table 4 summarizes changes in vital signs and weight that were recorded in the adult study (N=218) of Focalin XR in the treatment of ADHD.

Table 4. Changes (Mean ± SD) in Vital Signs and Weight by Randomized Dose during Double-Blind Treatment – Adults
 | Focalin XR 20 mg (N=57) | Focalin XR 30 mg (N=54) | Focalin XR 40 mg (N=54) | Placebo (N=53)
Pulse (bpm) | 3.1 ± 11.1 | 4.3 ± 11.7 | 6.0 ± 10.1 | -1.4 ± 9.3
Diastolic BP (mmHg) | -0.2 ± 8.2 | 1.2 ± 8.9 | 2.1 ± 8.0 | 0.3 ± 7.8
Weight (kg) | -1.4 ± 2.0 | -1.2 ± 1.9 | -1.7 ± 2.3 | -0.1 ± 3.9

6.5 Adverse Events with Other Methylphenidate HCl Dosage Forms

Nervousness and insomnia are the most common adverse reactions reported with other methylphenidate products. In children, loss of appetite, abdominal pain, weight loss during prolonged therapy, insomnia, and tachycardia may occur more frequently; however, any of the other adverse reactions listed below may also occur.

Other reactions include:

Cardiac: angina, arrhythmia, palpitations, pulse increased or decreased, tachycardia

Gastrointestinal: abdominal pain, nausea

Immune: hypersensitivity reactions including skin rash, urticaria, fever, arthralgia, exfoliative dermatitis, erythema multiforme with histopathological findings of necrotizing vasculitis, and thrombocytopenic purpura

Metabolism/Nutrition: anorexia, weight loss during prolonged therapy

Nervous System: dizziness, drowsiness, dyskinesia, headache, rare reports of Tourette’s syndrome, toxic psychosis

Vascular: blood pressure increased or decreased, cerebral arteritis and/or occlusion

Although a definite causal relationship has not been established, the following have been reported in patients taking methylphenidate:

Blood/Lymphatic: leukopenia and/or anemia

Hepatobiliary: abnormal liver function, ranging from transaminase elevation to hepatic coma

Psychiatric: transient depressed mood, aggressive behavior

Skin/Subcutaneous: scalp hair loss

Very rare reports of neuroleptic malignant syndrome (NMS) have been received, and, in most of these, patients were concurrently receiving therapies associated with NMS. In a single report, a ten-year-old boy who had been taking methylphenidate for approximately 18 months experienced an NMS-like event within 45 minutes of ingesting his first dose of venlafaxine. It is uncertain whether this case represented a drug-drug interaction, a response to either drug alone, or some other cause.

7 DRUG INTERACTIONS

Focalin XR should not be used in patients being treated (currently or within the preceding two weeks) with MAO Inhibitors [see Contraindications (4.5)].

Because of possible effects on blood pressure, Focalin XR should be used cautiously with pressor agents.

Methylphenidate may decrease the effectiveness of drugs used to treat hypertension.

Dexmethylphenidate is metabolized primarily to d-ritalinic acid by de-esterification and not through oxidative pathways.

The effects of gastrointestinal pH alterations on the absorption of dexmethylphenidate from Focalin XR have not been studied. Since the modified release characteristics of Focalin XR are pH dependent, the coadministration of antacids or acid suppressants could alter the release of dexmethylphenidate.

Human pharmacologic studies have shown that racemic methylphenidate may inhibit the metabolism of coumarin anticoagulants, anticonvulsants (e.g., phenobarbital, phenytoin, primidone), and tricyclic drugs (e.g., imipramine, clomipramine, desipramine). Downward dose adjustments of these drugs may be required when given concomitantly with methylphenidate. It may be necessary to adjust the dosage and monitor plasma drug concentration (or, in the case of coumarin, coagulation times), when initiating or discontinuing methylphenidate.

8 USE IN SPECIFIC POPULATIONS

8.1 Pregnancy

Pregnancy Category C:

There are no adequate and well controlled studies of Focalin in pregnant women. Dexmethylphenidate did not cause major malformations in rats or rabbits; however, it did cause delayed skeletal ossification and decreased postweaning weight gain in rats. Focalin XR should be used during pregnancy only if the potential benefit justifies the potential risk to the fetus.

In studies conducted in rats and rabbits, dexmethylphenidate was administered orally at doses of up to 20 and 100 mg/kg/day, respectively, during the period of organogenesis. No evidence of teratogenic activity was found in either the rat or rabbit study; however, delayed fetal skeletal ossification was observed at the highest dose level in rats. When dexmethylphenidate was administered to rats throughout pregnancy and lactation at doses of up to 20 mg/kg/day, postweaning body weight gain was decreased in male offspring at the highest dose, but no other effects on postnatal development were observed. At the highest doses tested, plasma levels (AUCs) of dexmethylphenidate in pregnant rats and rabbits were approximately 5 and 1 times, respectively, those in adults dosed with 20 mg/day.

Racemic methylphenidate has been shown to have teratogenic effects in rabbits when given in doses of 200 mg/kg/day throughout organogenesis.

8.2 Labor and Delivery

Focalin XR has not been studied in labor and delivery.

8.3 Nursing Mothers

It is not known whether dexmethylphenidate is excreted in human milk. Because many drugs are excreted in human milk, caution should be exercised if Focalin XR is administered to a nursing woman. Information from 4 published case reports on the use of racemic methylphenidate during breastfeeding suggest that at maternal doses of 35-80 mg/day, milk concentrations of methylphenidate range from undetectable to 15.4 ng/mL. Based on these limited data, the calculated infant daily dose for an exclusively breastfed infant would be about 0.4 – 2.9 µg/kg/day or about 0.2-0.7% of the maternal weight adjusted dose.

8.4 Pediatric Use

The safety and efficacy of Focalin XR in children under 6 years old have not been established. Long-term effects of Focalin in children have not been well established [see Warnings and Precautions (5.11)].

In a study conducted in young rats, racemic methylphenidate was administered orally at doses of up to 100 mg/kg/day for 9 weeks, starting early in the postnatal period (Postnatal Day 7) and continuing through sexual maturity (Postnatal Week 10). When these animals were tested as adults (Postnatal Weeks 13-14), decreased spontaneous locomotor activity was observed in males and females previously treated with 50 mg/kg/day (approximately 6 times the maximum recommended human dose [MRHD] of racemic methylphenidate on a mg/m^2 basis) or greater, and a deficit in the acquisition of a specific learning task was seen in females exposed to the highest dose (12 times the racemic MRHD on a mg/m^2 basis). The no effect level for juvenile neurobehavioral development in rats was 5 mg/kg/day (half the racemic MRHD on a mg/m^2 basis). The clinical significance of the long-term behavioral effects observed in rats is unknown.

8.5 Geriatric Use

Focalin XR has not been studied in the geriatric population.

9 DRUG ABUSE AND DEPENDENCE

9.1 Controlled Substance Class

Focalin XR, like other methylphenidate products, is classified as a Schedule II controlled substance by Federal regulation.

9.2 Abuse, Dependence, Tolerance

See complete boxed warning for drug abuse and dependence information at the beginning of Full Prescribing Information.

10 OVERDOSAGE

10.1 Signs and Symptoms

Signs and symptoms of acute methylphenidate overdosage, resulting principally from overstimulation of the CNS and from excessive sympathomimetic effects, may include the following: vomiting, agitation, tremors, hyperreflexia, muscle twitching, convulsions (may be followed by coma), euphoria, confusion, hallucinations, delirium, sweating, flushing, headache, hyperpyrexia, tachycardia, palpitations, cardiac arrhythmias, hypertension, mydriasis, and dryness of mucous membranes.

10.2 Poison Control Center

The physician may wish to consider contacting a poison control center for up-to-date information on the management of overdosage with methylphenidate.

10.3 Recommended Treatment

As with the management of all overdosage, the possibility of multiple drug ingestion should be considered.

When treating overdose, practitioners should bear in mind that there is a prolonged release of dexmethylphenidate from Focalin XR.

Treatment consists of appropriate supportive measures. The patient must be protected against self-injury and against external stimuli that would aggravate overstimulation already present. Gastric contents may be evacuated by gastric lavage as indicated. Before performing gastric lavage, control agitation and seizures if present and protect the airway. Other measures to detoxify the gut include administration of activated charcoal and a cathartic. Intensive care must be provided to maintain adequate circulation and respiratory exchange; external cooling procedures may be required for hyperpyrexia.

Efficacy of peritoneal dialysis for Focalin overdosage has not been established.

11 DESCRIPTION

Focalin XR is an extended-release formulation of dexmethylphenidate with a bi-modal release profile. Focalin XR uses the proprietary SODAS (Spheroidal Oral Drug Absorption System) technology. Each bead-filled Focalin XR capsule contains half the dose as immediate-release beads and half as enteric-coated, delayed-release beads, thus providing an immediate release of dexmethylphenidate and a second delayed release of dexmethylphenidate. Focalin XR is available as 5, 10, 15, 20, 25, 30, 35, and 40 mg extended-release capsules. Focalin XR 5, 10, 15, 20, 25, 30, 35, and 40 mg extended-release capsules provide in a single dose the same amount of dexmethylphenidate as dosages of 2.5, 5, 7.5, 10, 12.5, 15, 17.5, or 20 mg of Focalin given b.i.d. as tablets.

Dexmethylphenidate hydrochloride, the d-threo enantiomer of racemic methylphenidate hydrochloride, is a central nervous system (CNS) stimulant.

Dexmethylphenidate hydrochloride is methyl α-phenyl-2-piperidineacetate hydrochloride, (R,R’)-(+)-. Its empirical formula is C14H19NO2•HCl. Its molecular weight is 269.77 and its structural formula is

Note* = asymmetric carbon center

Dexmethylphenidate hydrochloride is a white to off white powder. Its solutions are acid to litmus. It is freely soluble in water and in methanol, soluble in alcohol, and slightly soluble in chloroform and in acetone.

Inactive ingredients: ammonio methacrylate copolymer, FD&C Blue #2 (5 mg, 15 mg, 25 mg, 35 mg, and 40 mg strengths), FDA/E172 yellow iron oxide (10 mg, 15 mg, 30 mg, 35 mg, and 40 mg strengths), gelatin, ink Tan SW-8010, methacrylic acid copolymer, polyethylene glycol, sugar spheres, talc, titanium dioxide, and triethyl citrate.

12 CLINICAL PHARMACOLOGY

12.1 Mechanism of Action

Dexmethylphenidate hydrochloride, the active ingredient in Focalin XR, is a central nervous system stimulant. Dexmethylphenidate, the more pharmacologically active d-enantiomer of racemic methylphenidate, is thought to block the reuptake of norepinephrine and dopamine into the presynaptic neuron and increase the release of these monoamines into the extraneuronal space. The mode of therapeutic action in Attention Deficit Hyperactivity Disorder (ADHD) is not known.

12.2 Pharmacodynamics

Effects on QT Interval

The effect of Focalin® XR on the QT interval was evaluated in a double-blind, placebo- and open label active (moxifloxacin)-controlled study following single doses of Focalin® XR 40mg in 75 healthy volunteers. ECGs were collected up to 12 h post-dose. Frederica’s method for heart rate correction was employed to derive the corrected QT interval (QTcF). The maximum mean prolongation of QTcF intervals was <5 ms, and the upper limit of the 90% confidence interval was below 10 ms for all time matched comparisons versus placebo. This was below the threshold of clinical concern and there was no evident-exposure response relationship.

12.3 Pharmacokinetics

Absorption

Focalin XR produces a bi-modal plasma concentration-time profile (i.e., two distinct peaks approximately 4 hours apart) when orally administered to healthy adults. The initial rate of absorption for Focalin XR is similar to that of Focalin tablets as shown by the similar rate parameters between the two formulations, i.e., first peak concentration (Cmax1), and time to the first peak (tmax1), which is reached in 1 ½ hours (typical range 1-4 hours). The mean time to the interpeak minimum (tminip) is slightly shorter, and time to the second peak (tmax2) is slightly longer for Focalin XR given once daily (about 6.5 hours, range 4.5-7 hours) compared to Focalin tablets given in two doses 4 hours apart (see Figure 1), although the ranges observed are greater for Focalin XR.

Focalin XR given once daily exhibits a lower second peak concentration (Cmax2), higher interpeak minimum concentrations (Cminip), and less peak and trough fluctuations than Focalin tablets given in two doses given 4 hours apart. This is due to an earlier onset and more prolonged absorption from the delayed-release beads (see Figure 1).

The AUC (exposure) after administration of Focalin XR given once daily is equivalent to the same total dose of Focalin tablets given in two doses 4 hours apart. The variability in Cmax, Cmin, and AUC is similar between Focalin XR and Focalin IR with approximately a three-fold range in each.

Radiolabeled racemic methylphenidate is well absorbed after oral administration with approximately 90% of the radioactivity recovered in urine. However, due to first pass metabolism the mean absolute bioavailability of dexmethylphenidate when administered in various formulations was 22-25%.

Figure 1 Mean Dexmethylphenidate Plasma Concentration-Time Profiles After Administration of 1 x 20 mg Focalin XR (n=24) Capsules and 2 x 10 mg Focalin Immediate-Release Tablets (n=25)

Dose Proportionality

Dose proportionality of Focalin XR was evaluated in a randomized, single-dose, five-period, cross-over study with administration of single doses of 5, 10, 20, 30 and 40 mg to healthy adults. Results confirmed dose proportionality within this dose range.

Food Effects

Administration times relative to meals and meal composition may need to be individually titrated.

No food effect study was performed with Focalin XR. However, the effect of food has been studied in adults with racemic methylphenidate in the same type of extended-release formulation. The findings of that study are considered applicable to Focalin XR. After a high fat breakfast, there was a longer lag time until absorption began and variable delays in the time until the first peak concentration, the time until the interpeak minimum, and the time until the second peak. The first peak concentration and the extent of absorption were unchanged after food relative to the fasting state, although the second peak was approximately 25% lower. The effect of a high fat lunch was not examined. There is no evidence of dose dumping in the presence or absence of food. There were no differences in the plasma concentration-time profile, when administered with applesauce, compared to administration in the fasting condition. The results are expected not to differ for Focalin XR.

For patients unable to swallow the capsule, the contents may be sprinkled on applesauce and administered [see Dosage and Administration (2)].

Distribution

The plasma protein binding of dexmethylphenidate is not known; racemic methylphenidate is bound to plasma proteins by 12-15%, independent of concentration. Dexmethylphenidate shows a volume of distribution of 2.65±1.11 L/kg. Plasma dexmethylphenidate concentrations decline monophasically following oral administration of Focalin XR.

Metabolism and Excretion

In humans, dexmethylphenidate is metabolized primarily to d-α-phenyl-piperidine acetic acid (also known as d-ritalinic acid) by de-esterification. This metabolite has little or no pharmacological activity. There is no in vivo interconversion to the l-threo-enantiomer, based on a finding of no levels of l-threo-methylphenidate being detectable after administration of up to 40 mg dexmethylphenidate in adults. After oral dosing of radiolabeled racemic methylphenidate in humans, about 90% of the radioactivity was recovered in urine. The main urinary metabolite of racemic (d,l-) methylphenidate was d,l-ritalinic acid, accountable for approximately 80% of the dose. Urinary excretion of parent compound accounted for 0.5% of an intravenous dose.

In vitro studies showed that dexmethylphenidate did not inhibit cytochrome P450 isoenzymes at concentrations observed after therapeutic doses.

Intravenous dexmethylphenidate was eliminated with a mean clearance of 0.40±0.12 L/kg.h^-1 corresponding to 0.56±0.18 L/min. The mean terminal elimination half-life of dexmethylphenidate was just over 3 hours in healthy adults and typically varied between 2 and 4.5 hours with an occasional subject exhibiting a terminal half-life between 5 and 7 hours. Children tend to have slightly shorter half-lives with means of 2–3 hours.

Special Populations

Gender

After administration of Focalin XR the first peak, (Cmax1), was on average 45% higher in women. The interpeak minimum and the second peak also tended to be slightly higher in women although the difference was not statistically significant, and these patterns remained even after weight normalization. Pharmacokinetic parameters for dexmethylphenidate after Focalin immediate-release tablets were similar for boys and girls.

Race

There is insufficient experience with the use of Focalin XR to detect ethnic variations in pharmacokinetics.

Age

The pharmacokinetics of dexmethylphenidate after Focalin XR administration have not been studied in children less than 18 years of age. When a similar formulation of racemic methylphenidate was examined in 15 children between 10 and 12 years of age and 3 children with ADHD between 7 and 9 years of age, the time to the first peak was similar, although the time until the between peak minimum, and the time until the second peak were delayed and more variable in children compared to adults. After administration of the same dose to children and adults, concentrations in children were approximately twice the concentrations observed in adults. This higher exposure is almost completely due to smaller body size as no relevant age-related differences in dexmethylphenidate pharmacokinetic parameters (i.e., clearance and volume of distribution) are observed after normalization to dose and weight.

Renal Insufficiency

There is no experience with the use of Focalin XR in patients with renal insufficiency. After oral administration of radiolabeled racemic methylphenidate in humans, methylphenidate was extensively metabolized and approximately 80% of the radioactivity was excreted in the urine in the form of racemic ritalinic acid which is pharmacologically inactive. Very little unchanged drug is excreted in the urine, thus renal insufficiency is expected to have little effect on the pharmacokinetics of Focalin XR.

Hepatic Insufficiency

There is no experience with the use of Focalin XR in patients with hepatic insufficiency (see Drug Interactions (7).

13 NONCLINICAL TOXICOLOGY

13.1 Carcinogenesis, Mutagenesis, and Impairment of Fertility

Carcinogenesis

Lifetime carcinogenicity studies have not been carried out with dexmethylphenidate. In a lifetime carcinogenicity study carried out in B6C3F1 mice, racemic methylphenidate caused an increase in hepatocellular adenomas, and in males only, an increase in hepatoblastomas at a daily dose of approximately 60 mg/kg/day. Hepatoblastoma is a relatively rare rodent malignant tumor type. There was no increase in total malignant hepatic tumors. The mouse strain used is sensitive to the development of hepatic tumors, and the significance of these results to humans is unknown.

Racemic methylphenidate did not cause any increase in tumors in a lifetime carcinogenicity study carried out in F344 rats; the highest dose used was approximately 45 mg/kg/day.

In a 24-week study of racemic methylphenidate in the transgenic mouse strain p53+/-, which is sensitive to genotoxic carcinogens, there was no evidence of carcinogenicity. Mice were fed diets containing the same concentrations as in the lifetime carcinogenicity study; the high-dose group was exposed to 60-74 mg/kg/day of racemic methylphenidate.

Mutagenesis

Dexmethylphenidate was not mutagenic in the in vitro Ames reverse mutation assay, the in vitro mouse lymphoma cell forward mutation assay, or the in vivo mouse bone marrow micronucleus test.

Racemic methylphenidate was not mutagenic in the in vitro Ames reverse mutation assay or the in vitro mouse lymphoma cell forward mutation assay, and was negative in vivo in the mouse bone marrow micronucleus assay. However, sister chromatid exchanges and chromosome aberrations were increased, indicative of a weak clastogenic response, in an in vitro assay of racemic methylphenidate in cultured Chinese Hamster Ovary (CHO) cells.

Impairment of Fertility

Racemic methylphenidate did not impair fertility in male or female mice that were fed diets containing the drug in an 18-week Continuous Breeding study. The study was conducted at doses of up to 160 mg/kg/day.

14 CLINICAL STUDIES

The effectiveness of Focalin XR in the treatment of ADHD was established in randomized, double-blind, placebo-controlled studies in children and adolescents and in adults who met Diagnostic and Statistical Manual 4th edition (DSM-IV) criteria for ADHD [see Indications and Usage (1)].

14.1 Children and Adolescents

The effectiveness of Focalin XR was established in a randomized, double-blind, placebo-controlled, parallel-group study in 103 pediatric patients (ages 6 to 12, n=86; ages 13 to 17, n=17) who met DSM-IV criteria for ADHD. Patients were randomized to receive either a flexible dose of Focalin XR (5 to 30 mg/day) or placebo once daily for 7 weeks. During the first 5 weeks of treatment patients were titrated to their optimal dose and in the last 2 weeks of the study patients remained on their optimal dose without dose changes or interruption.

Signs and symptoms of ADHD were evaluated by comparing the mean change from baseline to endpoint for Focalin XR– and placebo-treated patients using an intent-to-treat analysis of the primary efficacy outcome measure, the DSM-IV total subscale score of the Conners ADHD/DSM-IV Scales for teachers (CADS-T).

There was a statistically significant treatment effect in favor of Focalin XR. There were insufficient adolescents enrolled in this study to assess the efficacy for Focalin XR in the adolescent population. However, pharmacokinetic considerations and evidence of effectiveness of immediate-release Focalin in adolescents support the effectiveness of Focalin XR in this population.

In two additional studies in pediatric patients aged 6-12 years who received 20 mg Focalin XR or placebo in a cross-over design, Focalin XR was found to have a statistically significant treatment effect versus placebo on the Swanson, Kotkin, Agler, M-Flynn & Pelham (SKAMP) rating scale combined score at all time points after dosing in each study (0.5, 1, 3, 4, 5, 7, 9, 10, 11 and 12 hours in one study and 1, 2, 4, 6, 8, 9, 10, 11 and 12 hours in the other study). A treatment effect was also observed 0.5 hours after administration of Focalin XR 20 mg in an additional study of ADHD patients aged 6-12 years. The SKAMP is a reliable and validated scale that assesses specific classroom behaviors related to attention (e.g., getting started, sticking with activities, completing work, and stopping for transition) and deportment or behavior (e.g., remaining quiet, remaining seated, interacting with other students, and interacting with the teacher.) Each item is rated on a 7-point impairment scale, and an average rating per item is calculated for the subscales of Attention and Deportment.

14.2 Adults

The effectiveness of Focalin XR was established in a randomized, double-blind, placebo-controlled, parallel-group study in 221 adult patients (ages 18 to 60) who met DSM-IV criteria for ADHD. Patients were randomized to receive either a fixed dose of Focalin XR (20, 30, or 40 mg/day) or placebo once daily for 5 weeks. Patients randomized to Focalin XR were initiated on a 10 mg/day starting dose and titrated in increments of 10 mg/week to the randomly assigned fixed dose. Patients were maintained on their fixed dose (20, 30 or 40 mg/day) for a minimum of 2 weeks.

Signs and symptoms of ADHD were evaluated by comparing the mean change from baseline to endpoint for Focalin XR– and placebo-treated patients using an intent-to-treat analysis of the primary efficacy outcome measure, the investigator-administered DSM-IV Attention-Deficit/Hyperactivity Disorder Rating Scale (DSM-IV ADHD RS).

All three Focalin XR doses were statistically significantly superior to placebo. There was no obvious increase in effectiveness with increasing dose.

15 REFERENCES

American Psychiatric Association. Diagnosis and Statistical Manual of Mental Disorders. 4th ed. Washington DC: American Psychiatric Association 1994.

16 HOW SUPPLIED/STORAGE AND HANDLING

5 mg Extended-Release Capsules (NDC 0078-0430-05) light-blue, (imprinted NVR D5) supplied in bottles of 100

10 mg Extended-Release Capsules (NDC 0078-0431-05) light caramel (imprinted NVR D10) supplied in bottles of 100

15 mg Extended-Release Capsules (NDC 0078-0493-05) green (imprinted NVR D15) supplied in bottles of 100

20 mg Extended-Release Capsules (NDC 0078-0432-05) white (imprinted NVR D20) supplied in bottles of 100

25 mg Extended-Release Capsules (NDC 0078-0608-05) light-blue and white (imprinted NVR D25) supplied in bottles of 100

30 mg Extended-Release Capsules (NDC 0078-0433-05) light caramel and white (imprinted NVR D30) supplied in bottles of 100

35 mg Extended-Release Capsules (NDC 0078-0609-05) light-blue and light caramel (imprinted NVR D35) supplied in bottles of 100

40 mg Extended-Release Capsules (NDC 0078-0434-05) green and white (imprinted NVR D40) supplied in bottles of 100

Store FOCALIN XR at 25°C (77°F), excursions permitted 15°-30°C (59°-86°F). [See USP Controlled Room Temperature.]

Dispense in tight container (USP).

17 PATIENT COUNSELING INFORMATION

INFORMATION FOR PATIENTS

Prescribers or other health professionals should inform patients, their families, and their caregivers about the benefits and risks associated with treatment with dexmethylphenidate and should counsel them in its appropriate use. A patient Medication Guide is available for Focalin XR. The prescriber or health professional should instruct patients, their families, and their caregivers to read the Medication Guide and should assist them in understanding its contents. Patients should be given the opportunity to discuss the contents of the Medication Guide and to obtain answers to any questions they may have. The complete text of the Medication Guide is reprinted at the end of this document.

T2011-58

MEDICATION GUIDE

FOCALIN XR

(dexmethylphenidate hydrochloride) extended-release capsules CII

Read the Medication Guide that comes with FOCALIN XR before you or your child starts taking it and each time you get a refill. There may be new information. This Medication Guide does not take the place of talking to your doctor about your or your child’s treatment with FOCALIN XR.

What is the most important information I should know about FOCALIN XR?

The following have been reported with use of dexmethylphenidate hydrochloride and other stimulant medicines.
1. Heart-related problems:

- sudden death in patients who have heart problems or heart defects
- stroke and heart attack in adults
- increased blood pressure and heart rate

Tell your doctor if you or your child have any heart problems, heart defects, high blood pressure, or a family history of these problems.
Your doctor should check you or your child carefully for heart problems before starting FOCALIN XR.
Your doctor should check your or your child’s blood pressure and heart rate regularly during treatment with FOCALIN XR.
Call your doctor right away if you or your child has any signs of heart problems such as chest pain, shortness of breath, or fainting while taking FOCALIN XR.
2. Mental (Psychiatric) problems:
All Patients

- new or worse behavior and thought problems
- new or worse bipolar illness
- new or worse aggressive behavior or hostility

Children and Teenagers

- new psychotic symptoms (such as hearing voices, believing things that are not true, are suspicious) or new manic symptoms

Tell your doctor about any mental problems you or your child have, or about a family history of suicide, bipolar illness, or depression.
Call your doctor right away if you or your child have any new or worsening mental symptoms or problems while taking FOCALIN XR, especially seeing or hearing things that are not real, believing things that are not real, or are suspicious.

What Is FOCALIN XR?

FOCALIN XR is a central nervous system stimulant prescription medicine. It is used for the treatment of attention deficit and hyperactivity disorder (ADHD). FOCALIN XR may help increase attention and decrease impulsiveness and hyperactivity in patients with ADHD.

FOCALIN XR should be used as a part of a total treatment program for ADHD that may include counseling or other therapies.

FOCALIN XR is a federally controlled substance (CII) because it can be abused or lead to dependence. Keep FOCALIN XR in a safe place to prevent misuse and abuse. Selling or giving away FOCALIN XR may harm others, and is against the law.
Tell your doctor if you or your child have (or have a family history of) ever abused or been dependent on alcohol, prescription medicines or street drugs

Who should not take FOCALIN XR?

FOCALIN XR should not be taken if you or your child:

- are very anxious, tense, or agitated
- have an eye problem called glaucoma
- have tics or Tourette’s syndrome, or a family history of Tourette’s syndrome. Tics are hard to control repeated movements or sounds.
- are taking or have taken within the past 14 days an anti-depression medicine called a monoamine oxidase inhibitor or MAOI.
- are allergic to anything in FOCALIN XR. See the end of this Medication Guide for a complete list of ingredients.

FOCALIN XR should not be used in children less than 6 years old because it has not been studied in this age group.

FOCALIN XR may not be right for you or your child. Before starting FOCALIN XR tell your or your child’s doctor about all health conditions (or a family history of) including:

- heart problems, heart defects, high blood pressure
- mental problems including psychosis, mania, bipolar illness, or depression
- tics or Tourette’s syndrome
- seizures or have had an abnormal brain wave test (EEG)

Tell your doctor if you or your child is pregnant, planning to become pregnant, or breast-feeding.

Can FOCALIN XR be taken with other medicines?

Tell your doctor about all of the medicines that you or your child take including prescription and nonprescription medicines, vitamins, and herbal supplements. FOCALIN XR and some medicines may interact with each other and cause serious side effects. Sometimes the doses of other medicines will need to be adjusted while taking FOCALIN XR.

Your doctor will decide whether FOCALIN XR can be taken with other medicines.

Especially tell your doctor if you or your child takes:

- anti-depression medicines including MAOIs
- seizure medicines
- blood thinner medicines
- blood pressure medicines
- antacids
- cold or allergy medicines that contain decongestants

Know the medicines that you or your child takes. Keep a list of your medicines with you to show your doctor and pharmacist.

Do not start any new medicine while taking FOCALIN XR without talking to your doctor first.

How should FOCALIN XR be taken?

- Take FOCALIN XR exactly as prescribed. Your doctor may adjust the dose until it is right for you or your child.
- Take FOCALIN XR once each day in the morning. FOCALIN XR is an extended-release capsule. It releases medicine into your body throughout the day.
- FOCALIN XR can be taken with or without food. Taking FOCALIN XR with food may slow the time it takes for the medicine to start working.
- Swallow FOCALIN XR capsules whole with water or other liquids. Do not chew, crush, or divide the capsules or the beads in the capsule. If you or your child cannot swallow the capsule, open it and sprinkle the small beads of medicine over a spoonful of applesauce and swallow it right away without chewing.
- From time to time, your doctor may stop FOCALIN XR treatment for a while to check ADHD symptoms.
- Your doctor may do regular checks of the blood, heart, and blood pressure while taking FOCALIN XR. Children should have their height and weight checked often while taking FOCALIN XR. FOCALIN XR treatment may be stopped if a problem is found during these check-ups.
- If you or your child takes too much FOCALIN XR or overdoses, call your doctor or poison control center right away, or get emergency treatment.

What are possible side effects of FOCALIN XR?

See “What is the most important information I should know about FOCALIN XR?” for information on reported heart and mental problems.

Other serious side effects include:

- slowing of growth (height and weight) in children
- seizures, mainly in patients with a history of seizures
- eyesight changes or blurred vision

Common side effects include:

- headache
- upset stomach
- trouble sleeping
- anxiety

- decreased appetite
- dry mouth
- dizziness
- nervousness

Talk to your doctor if you or your child has side effects that are bothersome or do not go away.

This is not a complete list of possible side effects. Ask your doctor or pharmacist for more information.

How should I store FOCALIN XR?

- Store FOCALIN XR in a safe place at room temperature, 59 to 86° F (15 to 30° C).
- Keep FOCALIN XR and all medicines out of the reach of children.

General information about FOCALIN XR

Medicines are sometimes prescribed for purposes other than those listed in a Medication Guide. Do not use FOCALIN XR for a condition for which it was not prescribed. Do not give FOCALIN XR to other people, even if they have the same condition. It may harm them and it is against the law.

This Medication Guide summarizes the most important information about FOCALIN XR. If you would like more information, talk with your doctor. You can ask your doctor or pharmacist for information about FOCALIN XR that was written for healthcare professionals. For more information about FOCALIN XR call 1-888-669-6682.

What are the ingredients in FOCALIN XR?

Active Ingredient: dexmethylphenidate hydrochloride

Inactive Ingredients: ammonio methacrylate copolymer, FD&C Blue #2 (5 mg, 15 mg, 25 mg, 35 mg, and 40 mg strengths), FDA/E172 yellow iron oxide (10 mg, 15 mg, 30 mg, 35 mg, and 40 mg strengths), gelatin, ink Tan SW-8010, methacrylic acid copolymer, polyethylene glycol, sugar spheres, talc, titanium dioxide, and triethyl citrate.

This Medication Guide has been approved by the U.S. Food and Drug Administration.

Focalin XR is a trademark of Novartis AG

SODAS® is a registered trademark of Elan Pharma International Ltd.

This product is covered by US patents including 5,837,284, 5,908,850, 6,228,398, 6,355,656, and 6,635,284.

Manufactured for

Novartis Pharmaceuticals Corporation

East Hanover, New Jersey 07936

By ELAN HOLDINGS INC.

Pharmaceutical Division

Gainesville, GA 30504

© Novartis

T2011-58/T2011-83

April 2011/April 2011